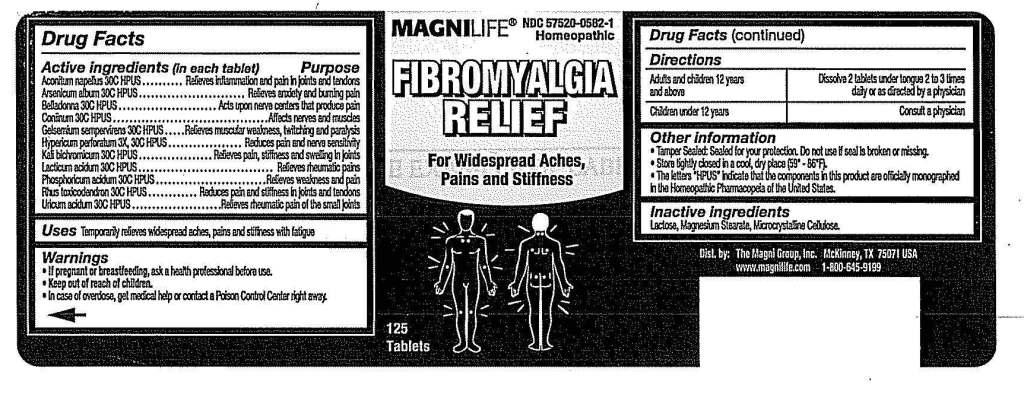 DRUG LABEL: Fibromyalgia Relief
NDC: 57520-0582 | Form: TABLET
Manufacturer: Apotheca Company
Category: homeopathic | Type: HUMAN OTC DRUG LABEL
Date: 20110607

ACTIVE INGREDIENTS: ACONITUM NAPELLUS 30 [hp_C]/1 1; ARSENIC TRIOXIDE 30 [hp_C]/1 1; ATROPA BELLADONNA 30 [hp_C]/1 1; CONIINE 30 [hp_C]/1 1; GELSEMIUM SEMPERVIRENS ROOT 30 [hp_C]/1 1; HYPERICUM PERFORATUM 30 [hp_C]/1 1; POTASSIUM DICHROMATE 30 [hp_C]/1 1; LACTIC ACID, DL- 30 [hp_C]/1 1; PHOSPHORIC ACID 30 [hp_C]/1 1; TOXICODENDRON PUBESCENS LEAF 30 [hp_C]/1 1; URIC ACID 30 [hp_C]/1 1
INACTIVE INGREDIENTS: LACTOSE; MAGNESIUM STEARATE; CELLULOSE, MICROCRYSTALLINE

Fibromyalgia Relief

ACTIVE INGREDIENT

ACTIVE INGREDIENS: Aconitum napellus 30C, Arsenicum album 30C, Belladonna 30C, Conniinum 30C, Gelsemium sempervirens 30C, Hypericum perforatum 3X, 30C, Kali bichromicum 30C, Lacticum acidum 30C, Phosphoricum acidum 30C, Rhus toxicodendron 30C, Uricum acidum 30C.

PURPOSE

USES: Temporarily relieves widespread aches, pains, and stiffness.

WARNINGS

WARNINGS: If pregnant or breastfeeding, ask a health professional before use.

Keep out of reach of children. In case of overdose, get medical help or contact a Poison Control Center right away.

OTHER INFORMATION: Tamper Sealed: Sealed for your protection. Do not use if seal is broken or missing.

Store tightly closed in a cool, dry place (59-86F).

The letters "HPUS" indicate that the components in this product are officially monographed in the Homeopathic Pharmacopeia of the United State.

DOSAGE AND ADMINISTRATION

DIRECTIONS: Adults and children 12 years and above: Dissolve 2 tablets under tongue 2 to 3 times daily or as directed by a physician.

Children under 12 years: Consult a physician.

INACTIVE INGREDIENT

INACTIVE INGREDIENTS: Lactose, Magnesium stearate, Microcrystalline cellulose.

KEEP OUT OF REACH OF CHILDREN. In case of overdose, get medical help or contact a Poison Control Center right away.

INDICATIONS AND USAGE

USES: Temporarily relieves widespread aches, pains, and stiffness.

QUESTIONS

Dist. by:

The Magni Group, Inc.

McKinney, TX 75071 USA

www.magnilife.com

1-800645-9199

PACKAGE LABEL

MAGNILIFE

NDC 57520-0582-1

Homeopathic

FIBROMYALGIA RELIEF

For widespread Aches, Pains and Stiffness

125 Tablets